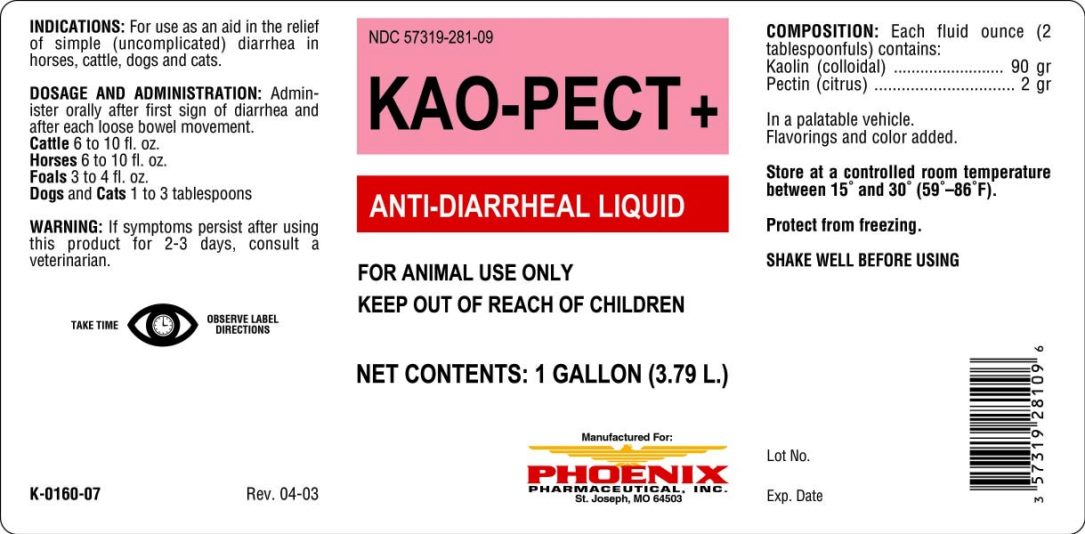 DRUG LABEL: KAO-PECT
NDC: 57319-281 | Form: SUSPENSION
Manufacturer: Clipper Distributing Company LLC
Category: animal | Type: OTC ANIMAL DRUG LABEL
Date: 20180319

ACTIVE INGREDIENTS: KAOLIN 5.8 g/29.57 mL; PECTIN 0.13 g/29.57 mL

KAO-PECT+

INDICATIONS AND USAGE

ANTI-DIARRHEAL LIQUID

FOR ANIMAL USE ONLY

KEEP OUT OF REACH OF CHILDREN

INDICATIONS

For use as an aid in the relief of simple (uncomplicated) diarrhea in horses, cattle, dogs and cats.

DOSAGE AND ADMINISTRATION

Administer orally after first sign of diarrhea and after each loose bowel movement.

Cattle 6 to 10 fl. ozs.

Horses 6 to 10 fl. ozs.

Foals 3 to 4 fl. ozs.

Dogs and Cats 1 to 3 tablespoons

WARNING

If symptoms persist after using this product for 2-3 days, consult a veterinarian.

COMPOSITION

Each fluid ounce (2 tablespoons) contains:

Kaolin (colloidal) ................................ 90 gr.

Pectin (citrus) .................................... 2 gr.

In a palatable vehicle. Flavorings and color added.

STORAGE AND HANDLING

Store in controlled room temperature between 15° and 30° (59°-86°).

Protect from freezing.

SHAKE WELL BEFORE USING

TAKE TIME OBSERVE LABEL DIRECTIONS